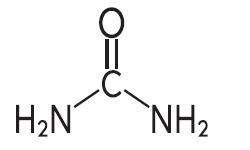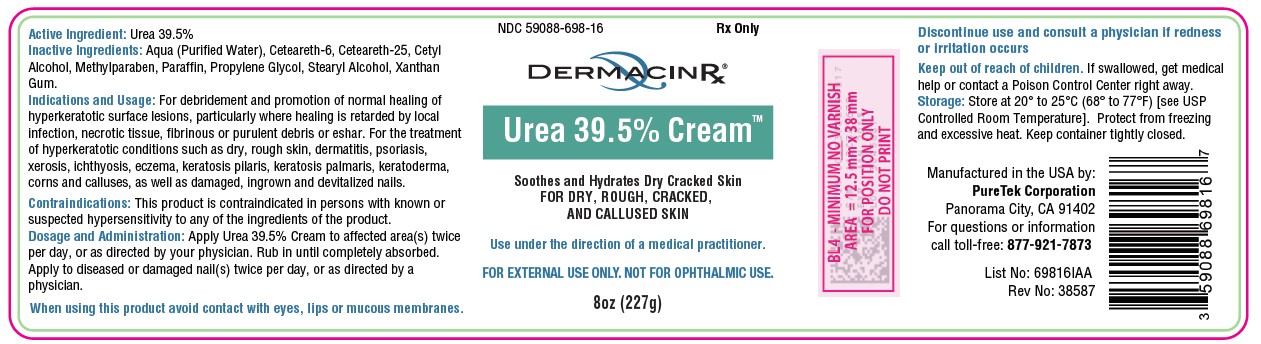 DRUG LABEL: Urea 39.5%
NDC: 59088-698 | Form: CREAM
Manufacturer: PureTek Corporation
Category: prescription | Type: HUMAN PRESCRIPTION DRUG LABEL
Date: 20230120

ACTIVE INGREDIENTS: UREA 395 mg/1 g
INACTIVE INGREDIENTS: CETEARETH-25; CETEARETH-6; CETYL ALCOHOL; METHYLPARABEN; PARAFFIN; PROPYLENE GLYCOL; WATER; STEARYL ALCOHOL; XANTHAN GUM

Urea 39.5% Cream Rx Only

DESCRIPTION

Urea 39.5% Cream is a keratolytic emollient which is a gentle, yet potent, tissue softener for nails and/or skin. Each gram contains 395 mg of urea in a vehicle consisting of: Aqua (Purified Water), Ceteareth-6, Ceteareth-25, Cetyl Alcohol, Methylparaben, Paraffin, Propylene Glycol, Stearyl Alcohol, Xanthan Gum.

Urea is a diamide of carbonic acid with the following chemical structure:

CLINICAL PHARMACOLOGY

Urea gently dissolves the intracellular matrix which results in loosening of the horny layer of the skin and shedding of scaly skin at regular intervals, thereby softening hyperkeratotic areas of the skin.

Pharmacokinetics

The mechanism of action of topically applied urea is not yet known.

INDICATIONS & USAGE

For debridement and promotion of normal healing of hyperkeratotic surface lesions, particularly where healing is retarded by local infection, necrotic tissue, ﬁbrinous or purulent debris or eshar. Urea is useful for the treatment of hyperkeratotic conditions such as dry, rough skin, dermatitis, psoriasis, xerosis, ichthyosis, eczema, keratosis pilaris, keratosis palmaris, keratoderma, corns and calluses, as well as damaged, ingrown and devitalized nails.

CONTRAINDICATIONS

This product is contraindicated in persons with known or suspected hypersensitivity to any of the ingredients of the product.

WARNINGS

FOREXTERNALUSEONLY. NOTFOR OPHTHALMIC USE. KEEP OUT OF REACH OF CHILDREN.

Avoid contact with eyes, lips and mucous membranes.

General

This product is to be used as directed by a physician and should not be used to treat any condition other than that for which it was prescribed. If redness or irritation occurs, discontinue use and consult a physician.

Information for Patients

Patients should discontinue the use of this product if the condition becomes worse or if a rash develops in the area being treated or elsewhere. Avoid contact with eyes, lips and mucous membranes.

Carcinogenesis, Mutagenesis and Impairment of Fertility:

Long-term animal studies for carcinogenic potential have not been performed on this product to date. Studies on reproduction and fertility also have not been performed.

Pregnancy:

Category C. Animal reproduction studies have not been conducted with this product. It is also not known whether this product can affect reproduction capacity or cause fetal harm when administered to a pregnant woman. This product should be used by a pregnant woman only if clearly needed or when potential benefits outweigh potential hazards to the fetus.

Nursing Mothers:

It is not known whether this drug is excreted in human milk. Because many drugs are excreted in human milk, caution should be exercised when this product is administered to a nursing woman.

ADVERSE REACTIONS:

Transient stinging, burning, itching or irritation may occur and normally disappear upon discontinuing the medication.

DOSAGE AND ADMINISTRATION

Apply Urea 39.5% to affected skin twice per day, or as directed by your physician. Rub in until completely absorbed.

Apply to diseased or damaged nail(s) twice per day, or as directed by a physician.

HOW SUPPLIED

Urea 39.5% Cream 8 oz. (227 g): NDC 59088-698-16

STORAGE

Store at 20° to 25°C (68° to 77°F) [see USP Controlled
Room Temperature]. Protect from freezing and excessive
heat. Keep container tightly closed.

KEEP THIS AND ALL MEDICATIONS OUT OF THE REACH OF CHILDREN.

Urea 39.5% Cream™

Manufactured in the USA by:
PureTek Corporation
Panorama City, CA 91402
For questions or information
call toll-free: 877-921-7873